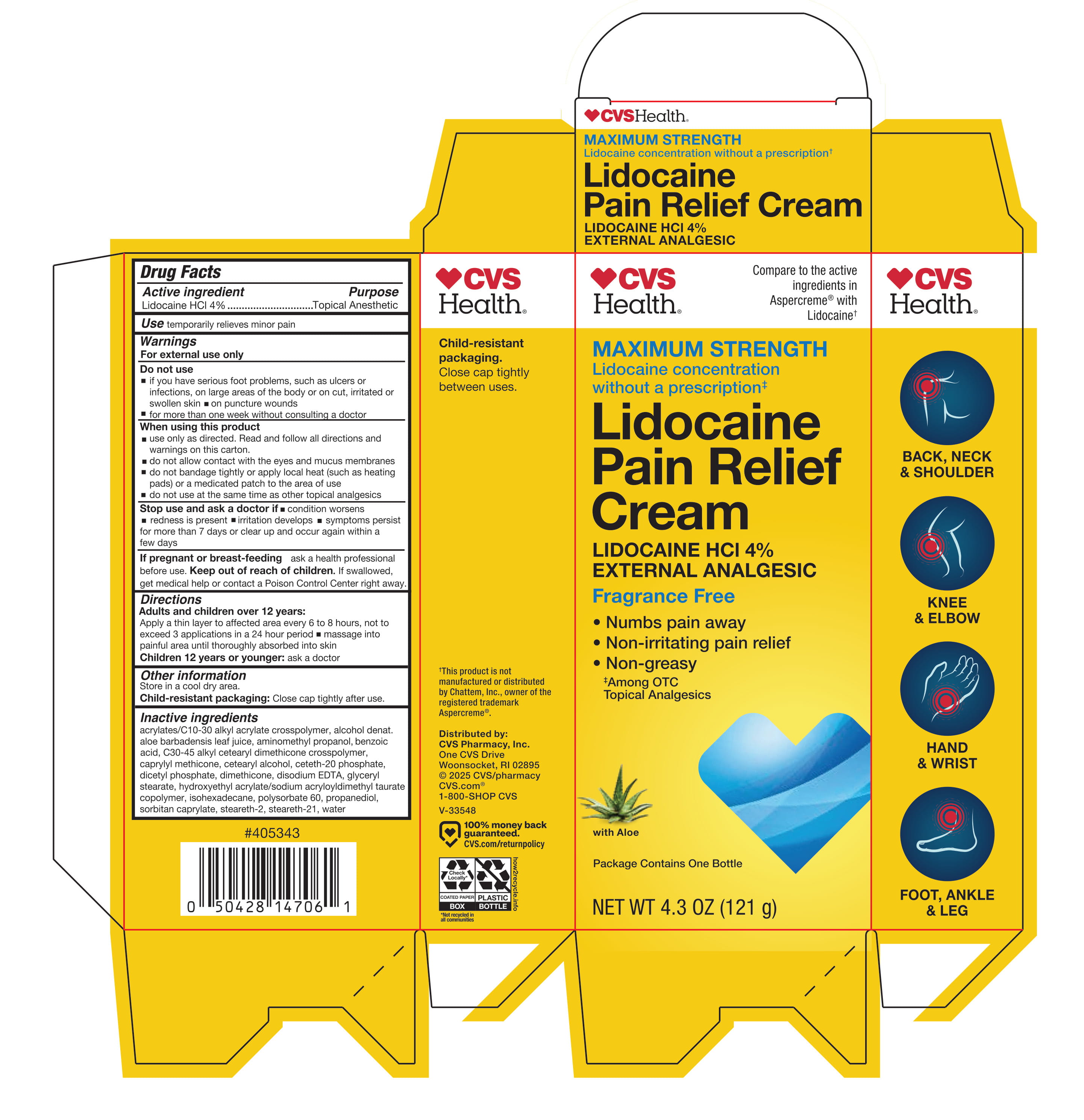 DRUG LABEL: CVS Lidocaine Pain Relief Cream
NDC: 51316-379 | Form: CREAM
Manufacturer: CVS Pharmacy
Category: otc | Type: HUMAN OTC DRUG LABEL
Date: 20260116

ACTIVE INGREDIENTS: LIDOCAINE HYDROCHLORIDE 40 mg/1 g
INACTIVE INGREDIENTS: PROPANEDIOL; BENZOIC ACID; ISOHEXADECANE; HYDROXYETHYL ACRYLATE/SODIUM ACRYLOYLDIMETHYL TAURATE COPOLYMER (45000 MPA.S AT 1%); STEARETH-21; C30-45 ALKYL CETEARYL DIMETHICONE CROSSPOLYMER; CAPRYLYL METHICONE; CETEARYL ALCOHOL; AMINOMETHYL PROPANOL; ACRYLATES/C10-30 ALKYL ACRYLATE CROSSPOLYMER (60000 MPA.S); DIMETHICONE; EDETATE DISODIUM; ALOE BARBADENSIS LEAF JUICE; SORBITAN CAPRYLATE; STEARETH-2; POLYSORBATE 60; WATER; ALCOHOL; CETETH-20 PHOSPHATE; DICETYL PHOSPHATE; GLYCERYL STEARATE

CVS Lidocaine Pain Relief Cream

Active ingredient

Lidocaine HCl 4%

Purpose

Topical Anesthetic

Use

Temporarily relieves minor pain

Warnings

For external use only

Do not use

- if you have serious foot problems, such as ulcers or infections
- on large areas of the body
- on cut, irritated or swollen skin
- on puncture wounds
- for more than one week without consulting a doctor

When using this product

- use only as directed. Read and follow all directions and warning on this carton.
- do not allow contact with the eyes and mucus membranes
- do not bandage tightly or apply local heat (such as heating pads) or a medicated patch to the area of use
- do not use at the same time as other topical analgesics

Stop use and ask a doctor if

- condition worsens
- redness is present
- irritation develops
- symptoms persist for more than 7 days or clear up and occur again within a few days

If pregnant or breast-feeding

ask a health professional before use.

Keep out of reach of children.

If swallowed, get medical help or contact a Poison Control Center right away.

Directions

Adults and children over 12 years:

- Apply a thin layer to affect area every 6 to 8 hours, not to exceed 3 applications in a 24 hour period.
- massage into painful area until thoroughly absorbed into skin

Children 12 years or younger: ask a doctor

Other information

Store in a cool dry area.

Child-resistant packaging: Close cap tightly after use.

Inactive ingredients

acrylates/C10-30 alkyl acrylate crosspolymer, alcohol denat., aloe barbadensis leaf juice, aminomethyl propanol, benzoic acid, C30-45 alkyl cetearyl dimethicone crosspolymer, caprylyl methicone, cetearyl alcohol, ceteth-20 phosphate, dicetyl phosphate, dimethicone, disodium EDTA, glyceryl stearate, hydroxyethyl acrylate/sodium acryloyldimethyl taurate copolymer, isohexadecane, polysorbate 60, propanediol, sorbitan caprylate, steareth-2, steareth-21, water

Principal Display Panel - 121 g Carton

CVS

Health®

Compare to the active ingredients in Aspercreme® with Lidocaine†

Maximum Strength

Lidocaine concentration without a prescription‡

Lidocaine Pain Relief Cream

Lidocaine HCl 4%

External analgesic

Fragrance Free

- Numbs pain away
- Non-irritating pain relief
- Non-greasy

‡Among OTC Topical Analgesics

with Aloe

Package Contains One Bottle

NET WT 4.3 OZ (121 g)